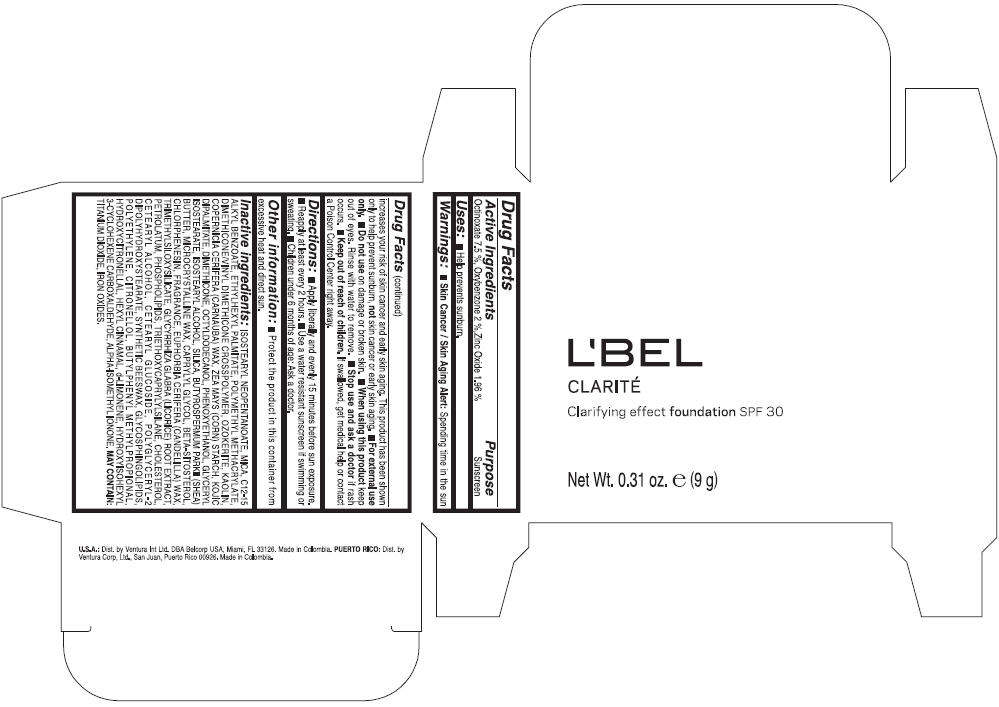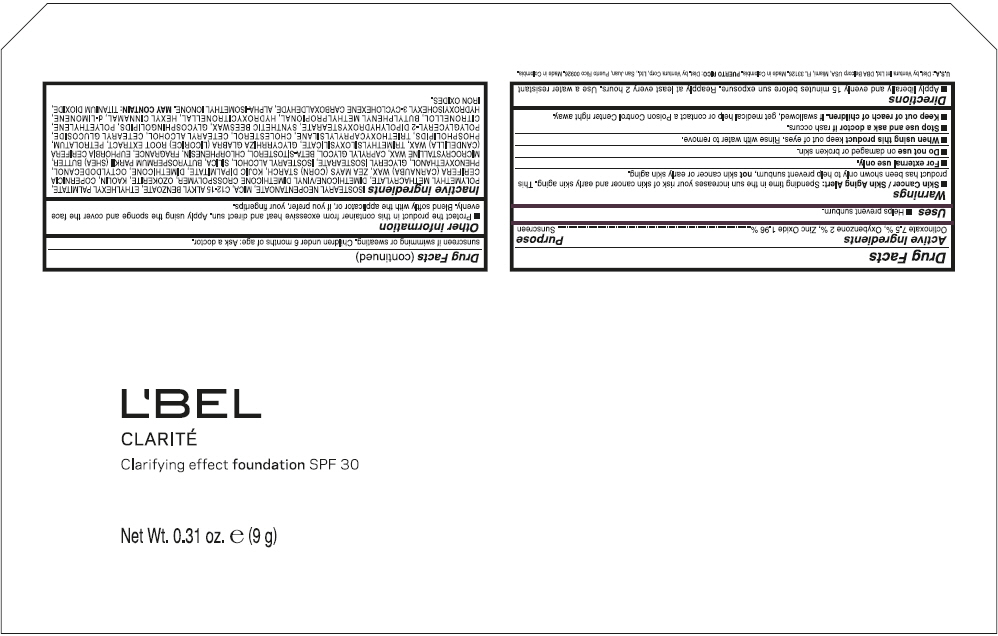 DRUG LABEL: LBEL CLARITE Clarifying Effect Foundation SPF 30 
NDC: 14141-943 | Form: SUSPENSION
Manufacturer: Bel Star S.A. (Colombia)
Category: otc | Type: HUMAN OTC DRUG LABEL
Date: 20191221

ACTIVE INGREDIENTS: Octinoxate 0.075 g/1 g; Oxybenzone 0.02 g/1 g; Zinc Oxide 0.0196 g/1 g
INACTIVE INGREDIENTS: ISOSTEARYL NEOPENTANOATE; MICA; ALKYL (C12-15) BENZOATE; ETHYLHEXYL PALMITATE; POLY(METHYL METHACRYLATE; 450000 MW); CERESIN; KAOLIN; CARNAUBA WAX; STARCH, CORN; KOJIC DIPALMITATE; DIMETHICONE; OCTYLDODECANOL; PHENOXYETHANOL; GLYCERYL ISOSTEARATE; ISOSTEARYL ALCOHOL; SILICON DIOXIDE; SHEA BUTTER; MICROCRYSTALLINE WAX; CAPRYLYL GLYCOL; .BETA.-SITOSTEROL; CHLORPHENESIN; CANDELILLA WAX; GLYCYRRHIZA GLABRA; PETROLATUM; LECITHIN, SOYBEAN; TRIETHOXYCAPRYLYLSILANE; CHOLESTEROL; CETOSTEARYL ALCOHOL; CETEARYL GLUCOSIDE; POLYGLYCERYL-2 DIPOLYHYDROXYSTEARATE; HIGH DENSITY POLYETHYLENE; TITANIUM DIOXIDE; FERRIC OXIDE YELLOW; FERRIC OXIDE RED; FERROSOFERRIC OXIDE

L'BEL CLARITÉ Clarifying Effect Foundation SPF 30

Drug Facts

ACTIVE INGREDIENT

Active Ingredients | Purpose
OCTINOXATE 7.50 % | Sunscreen
OXYBENZONE 2.00 % | Sunscreen
ZINC OXIDE 1.96 % | Sunscreen

Uses

- Helps prevent sunburn.

Warnings

- Skin Cancer / Skin Aging Alert: Spending time in the sun increases your risk of skin cancer and early skin aging. This product has been shown only to help prevent sunburn, not skin cancer or early skin aging.
- For external use only.

- Do not use on damaged or broken skin.

- When using this product keep out of eyes. Rinse with water to remove.

- Stop use and ask a doctor if rash occurs.

- Keep out of reach of children. If swallowed, get medical help or contact a Poison Control Center right away.

Directions

- Apply liberally and evenly 15 minutes before sun exposure.
- Reapply at least every 2 hours
- Use a water resistant sunscreen if swimming or sweating.
- Children under 6 months of age: Ask a doctor

Other information

- Protect the product in this container from excessive heat and direct sun.

Inactive ingredients

ISOSTEARYL NEOPENTANOATE, MICA, C12-15 ALKYL BENZOATE, ETHYLHEXYL PALMITATE, POLYMETHYL METHACRYLATE, DIMETHICONE/VINYL DIMETHICONE CROSSPOLYMER, OZOKERITE, KAOLIN, COPERNICIA CERIFERA CERA (COPERNICIA CERIFERA (CARNAUBA) WAX), ZEA MAYS STARCH (ZEA MAYS (CORN) STARCH), KOJIC DIPALMITATE, DIMETHICONE, OCTYLDODECANOL, PHENOXYETHANOL, GLYCERYL ISOSTEARATE, ISOSTEARYL ALCOHOL, SILICA, BUTYROSPERMUM PARKII BUTTER (BUTYROSPERMUM PARKII (SHEA) BUTTER), CERA MICROCRISTALLINA (MICROCRYSTALLINE WAX), CAPRYLYL GLYCOL, BETA-SITOSTEROL, CHLORPHENESIN, PARFUM (FRAGRANCE), CANDELILLA CERA (EUPHORBIA CERIFERA (CANDELILLA) WAX), TRIMETHYLSILOXYSILICATE, GLYCYRRHIZA GLABRA ROOT EXTRACT (GLYCYRRHIZA GLABRA (LICORICE) ROOT EXTRACT), PETROLATUM, PHOSPHOLIPIDS, TRIETHOXYCAPRYLYLSILANE, CHOLESTEROL, CETEARYL ALCOHOL, CETEARYL GLUCOSIDE, POLYGLYCERYL-2 DIPOLYHYDROXYSTEARATE, SYNTHETIC BEESWAX, GLYCOSPHINGOLIPIDS, POLYETHYLENE.

MAY CONTAIN : CI 77891 (TITANIUM DIOXIDE), CI 77492 (IRON OXIDES), CI 77491 (IRON OXIDES), CI 77499 (IRON OXIDES).

Dist. by Ventura Corp, Ltd., San Juan, Puerto Rico 00926.

PRINCIPAL DISPLAY PANEL - 9 g Case Box - CLAIRE 1- BEIGE

L'BEL
CLARITÉ
Clarifying effect foundation SPF 30

Net Wt. 0.31 oz. e (9 g)

PRINCIPAL DISPLAY PANEL - 9 g Case Box - CLAIRE 2- BEIGE

L'BEL
CLARITÉ
Clarifying effect foundation SPF 30

Net Wt. 0.31 oz. e (9 g)

PRINCIPAL DISPLAY PANEL - 9 g Case Box - CLAIRE 3- BEIGE

L'BEL
CLARITÉ
Clarifying effect foundation SPF 30

Net Wt. 0.31 oz. e (9 g)

PRINCIPAL DISPLAY PANEL - 9 g Case Box - CLAIRE 4- BEIGE

L'BEL
CLARITÉ
Clarifying effect foundation SPF 30

Net Wt. 0.31 oz. e (9 g)

PRINCIPAL DISPLAY PANEL - 9 g Case Box - MEDIUM 5- BEIGE

L'BEL
CLARITÉ
Clarifying effect foundation SPF 30

Net Wt. 0.31 oz. e (9 g)

PRINCIPAL DISPLAY PANEL - 9 g Case Box - MEDIUM 6- BEIGE

L'BEL
CLARITÉ
Clarifying effect foundation SPF 30

Net Wt. 0.31 oz. e (9 g)

PRINCIPAL DISPLAY PANEL - 9 g Case Box - MEDIUM 7- BEIGE

L'BEL
CLARITÉ
Clarifying effect foundation SPF 30

Net Wt. 0.31 oz. e (9 g)

PRINCIPAL DISPLAY PANEL - 9 g Case Box - OBSCURE 8- BROWN

L'BEL
CLARITÉ
Clarifying effect foundation SPF 30

Net Wt. 0.31 oz. e (9 g)

PRINCIPAL DISPLAY PANEL - 9 g Case Box - OBSCURE 9- BROWN

L'BEL
CLARITÉ
Clarifying effect foundation SPF 30

Net Wt. 0.31 oz. e (9 g)

PRINCIPAL DISPLAY PANEL - Kit Label

L'BEL

CLARITÉ

Clarifying effect foundation SPF 30

Net Wt. 0.31 oz. e (9 g)